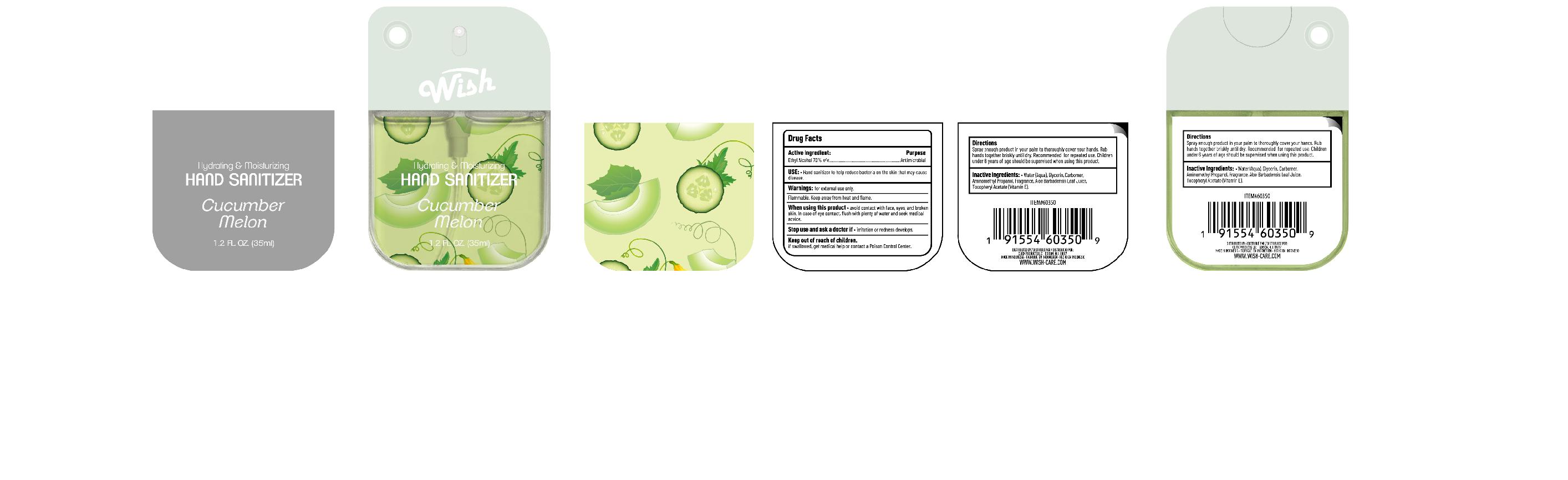 DRUG LABEL: HAND SANITIZER Cucumber Melon
NDC: 85537-150 | Form: SPRAY
Manufacturer: PT SUPER HOME PRODUCT INDONESIA
Category: otc | Type: HUMAN OTC DRUG LABEL
Date: 20260301

ACTIVE INGREDIENTS: ALCOHOL 70 mL/100 mL
INACTIVE INGREDIENTS: ALPHA-TOCOPHEROL ACETATE; AQUA; AMINOMETHYLPROPANOL; GLYCERIN; CARBOMER; FRAGRANCE CUCUMBER ALOE ORC1802955; ALOE BARBADENSIS LEAF JUICE

HAND SANITIZER Cucumber Melon

Active Ingredients:

Ethyl Alcohol 70% v/v Purpose: Antimicrobial

USE:

Hand sanitizer to help reduce bacteria on the skin that may cause disease.

Warnings:

For external use only. Flammable, keep away from fire or flame.

When using this product:

avoid contact with face, eyes, and broken skin.In case of eye contact, flush with plenty of water and seek medical advice.

Stop use and ask a doctor if:

Irritation or redness develops.

Keep out of reach of children:

lf swallowed, get medical help or contact a Poison Control Center.

Directions:

Spray onto hands and rub together until dry. Recommended for repeat use.children under 6 years of age should be superised when using this product.

Inactive Inaredients:

Water(Aqua), Glycerin,Carbomer,Aminomethyl Propanol,Fragrance,Aloe Barbadensis Leaf Juice,Tocophery Acetate(Vitamin E).